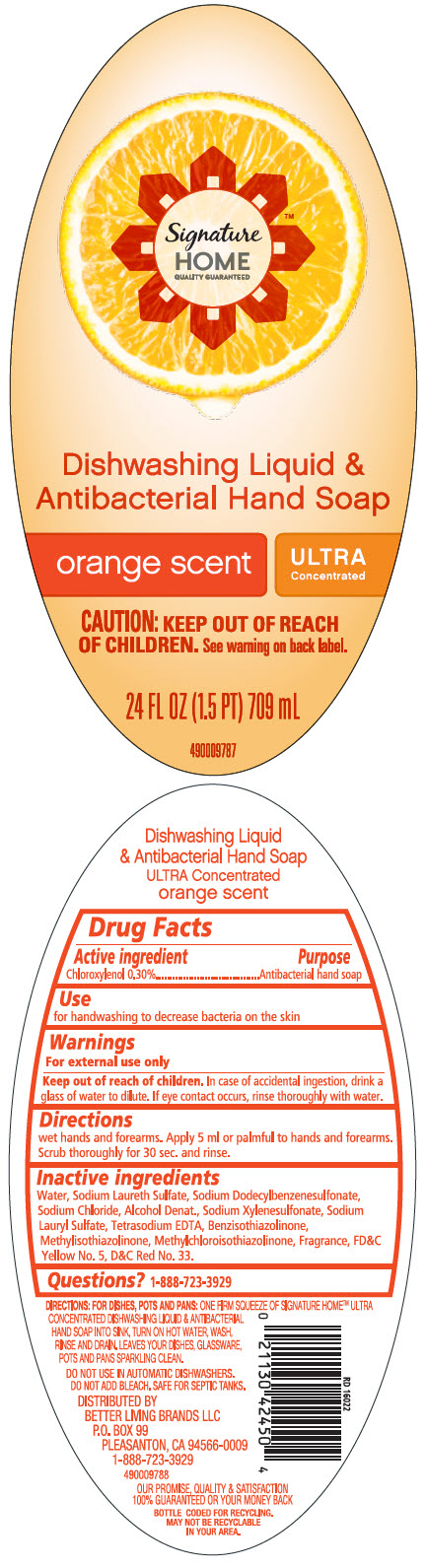 DRUG LABEL: Dishwashing Liquid and Antibacterial Hand 
NDC: 69560-123 | Form: SOLUTION
Manufacturer: Mid-Continent Packaging Inc.
Category: otc | Type: HUMAN OTC DRUG LABEL
Date: 20200114

ACTIVE INGREDIENTS: Chloroxylenol 0.3 g/100 mL
INACTIVE INGREDIENTS: WATER; ALCOHOL; SODIUM XYLENESULFONATE; SODIUM LAURYL SULFATE; EDETATE SODIUM; BENZISOTHIAZOLINONE; METHYLISOTHIAZOLINONE; FD&C YELLOW NO. 5; D&C RED NO. 33; SODIUM CHLORIDE; METHYLCHLOROISOTHIAZOLINONE; SODIUM LAURETH-3 SULFATE; SODIUM DODECYLBENZENESULFONATE

Dishwashing Liquid & Antibacterial Hand Soap
Orange Scent Ultra concentrated

Drug Facts

Active ingredient

Chloroxylenol 0.30%

Purpose

Antibacterial hand soap

Use

for handwashing to decrease bacteria on the skin

Warnings

For external use only

Keep out of reach of children. In case of accidental ingestion, drink a glass of water to dilute. If eye contact occurs, rinse thoroughly with water.

Directions

wet hands and forearms. Apply 5 ml or palmful to hands and forearms. Scrub thoroughly for 30 sec. and rinse.

Inactive ingredients

Water, Sodium Laureth Sulfate, Sodium Dodecylbenzenesulfonate, Sodium Chloride, Alcohol Denat., Sodium Xylenesulfonate, Sodium Lauryl Sulfate, Tetrasodium EDTA, Benzisothiazolinone, Methylisothiazolinone, Methylchloroisothiazolinone, Fragrance, FD&C Yellow No. 5, D&C Red No. 33.

Questions?

1-888-723-3929

DISTRIBUTED BY
BETTER LIVING BRANDS LLC
P.O. BOX 99
PLEASANTON, CA 94566-0009

PRINCIPAL DISPLAY PANEL - 709 mL Bottle Label

Signature™
HOME
QUALITY GUARANTEED

Dishwashing Liquid &
Antibacterial Hand Soap

orange scent
ULTRA
Concentrated

CAUTION: KEEP OUT OF REACH
OF CHILDREN. See warning on back label.

24 FL OZ (1.5 PT) 709 mL

490009787